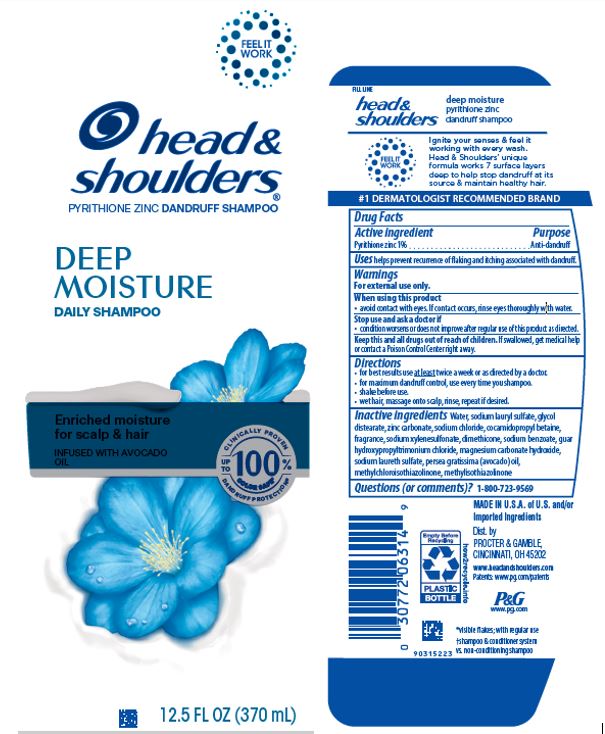 DRUG LABEL: Head and Shoulders Deep Moisture
NDC: 69423-247 | Form: SHAMPOO
Manufacturer: The Procter & Gamble Manufacturing Company
Category: otc | Type: HUMAN OTC DRUG LABEL
Date: 20251215

ACTIVE INGREDIENTS: PYRITHIONE ZINC 1 g/100 mL
INACTIVE INGREDIENTS: WATER; GUAR HYDROXYPROPYLTRIMONIUM CHLORIDE (1.7 SUBSTITUENTS PER SACCHARIDE); SODIUM LAURETH-3 SULFATE; SODIUM LAURYL SULFATE; DIMETHICONE; GLYCOL DISTEARATE; SODIUM XYLENESULFONATE; SODIUM CHLORIDE; SODIUM BENZOATE; METHYLCHLOROISOTHIAZOLINONE; METHYLISOTHIAZOLINONE; AVOCADO OIL; COCAMIDOPROPYL BETAINE; ZINC CARBONATE; MAGNESIUM CARBONATE HYDROXIDE

Head and Shoulders® Deep Moisture Shampoo
Old Spice Swagger

Drug Facts

Active ingredient

pyrithione zinc 1%

Purpose

Anti-dandruff

Uses

helps prevent recurrence of flaking and itching associated with dandruff.

Warnings

For external use only.

When using this product

- avoid contact with eyes. If contact occurs, rinse eyes thoroughly with water.

Stop use and ask a doctor if

- condition worsens or does not improve after regular use of this product as directed

KEEP OUT OF REACH OF CHILDREN

Keep this and all drugs out of reach of children. If swallowed, get medical help or contact a Poison Control Center right away.

Directions

- for best results use at least twice a week or as directed by a doctor.
- for maximum dandruff control, use every time you shampoo.
- shake before use.
- wet hair, massage onto scalp. Leave on for several minutes. Rinse. Repeat if desired.

Inactive Ingredients

Water, sodium lauryl sulfate, glycol distearate, zinc carbonate, sodium chloride, cocamidopropyl betaine, fragrance, sodium xylenesulfonate, dimethicone, sodium benzoate, guar hydroxypropyltrimonium chloride, magnesium carbonate hydroxide, sodium laureth sulfate, persea gratissima (avocado) oil, methylchloroisothiazolinone, methylisothiazolinone

Questions (or comments)?

1-800-723-9569

Dist. by PROCTER & GAMBLE,
CINCINNATI, OH 45202

PRINCIPAL DISPLAY PANEL - 370 mL Bottle Label

head &
shoulders®

pyrithione zinc dandruff shampoo

DEEP MOISTURE

DAILY SHAMPOO

enriched moisture for scalp & hair

INFUSED WITH AVOCADO OIL

12.5 FL OZ

(370 mL)